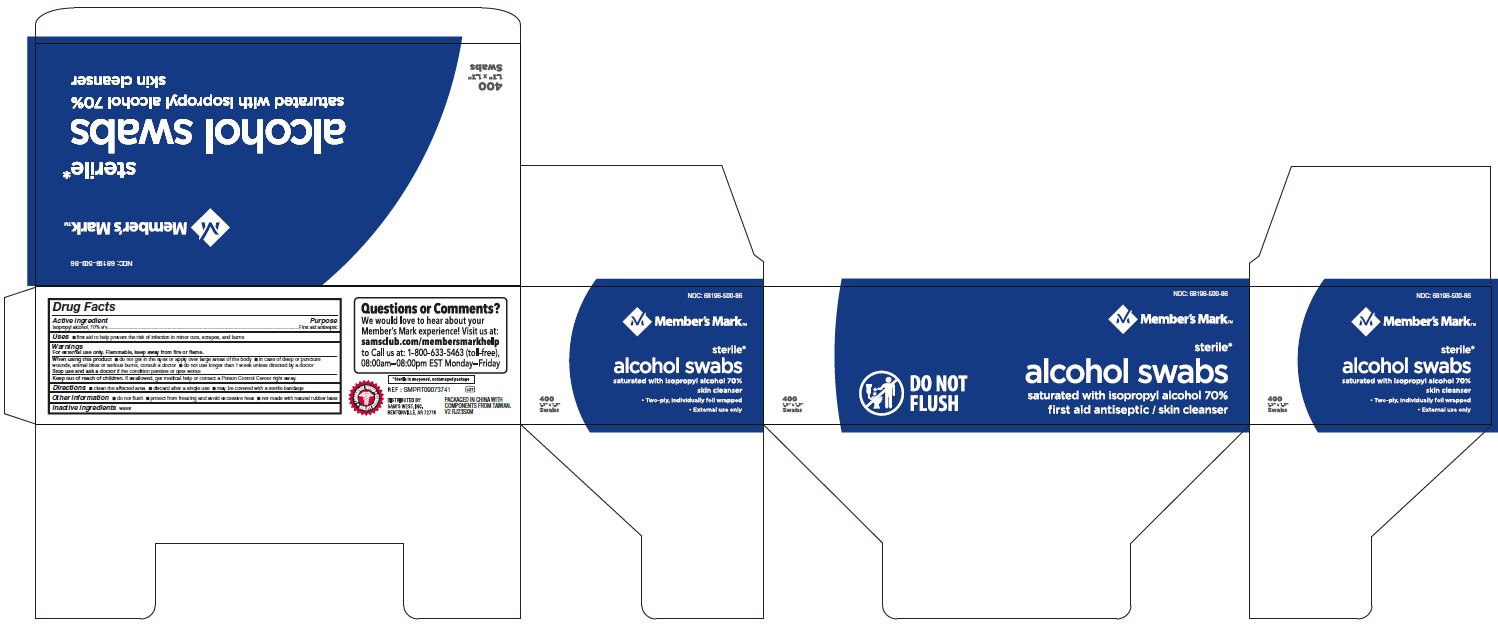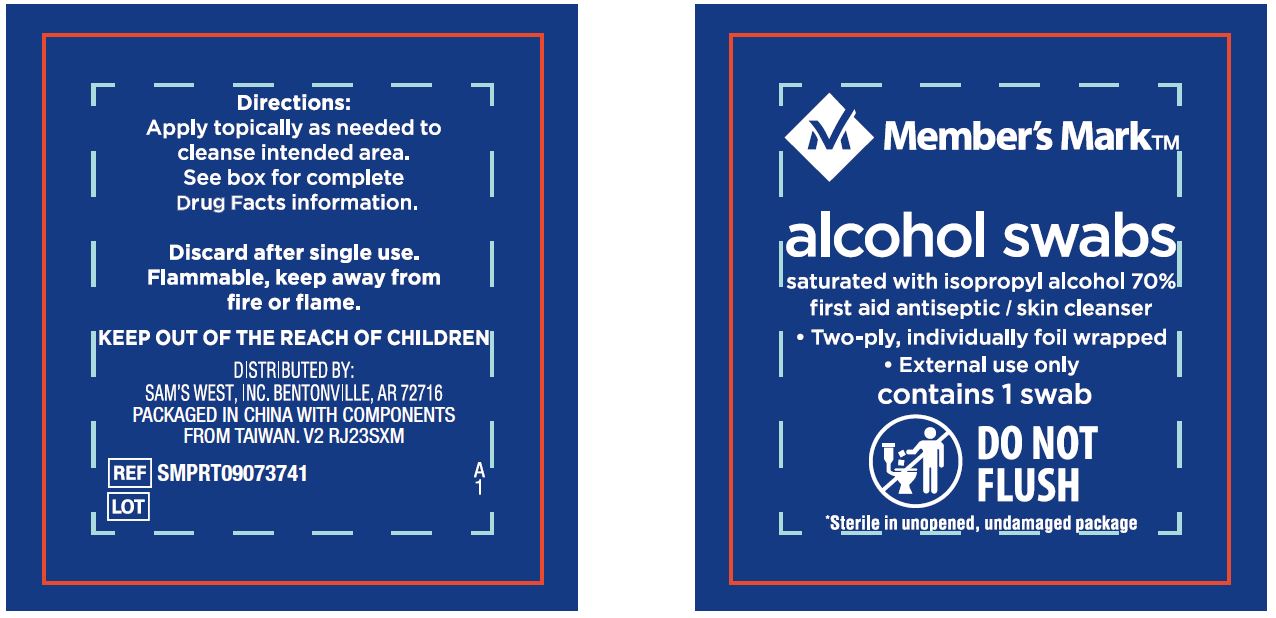 DRUG LABEL: Members Mark
NDC: 68196-500 | Form: SWAB
Manufacturer: Sams West Inc
Category: otc | Type: HUMAN OTC DRUG LABEL
Date: 20250103

ACTIVE INGREDIENTS: ISOPROPYL ALCOHOL 70 mL/100 mL
INACTIVE INGREDIENTS: WATER

68196-500 Sam's Club Alcohol Prep Pad

Active ingredient

Isopropyl alcohol 70% v/v

Purpose

first aid antiseptic

Uses

- first aid to help prevent the risk of skin infection in minor cuts, scrapes and burns

Warnings

For external use only.

Flammable, keep away from fire or flame.

When using this product

- do not get in the eyes or apply over large areas of the body
- in case of deep or puncture wounds, animal bites or serious burns, consult a doctor
- do not use longer than 1 week unless directed by a doctor

Stop use and ask a doctor if

- the condition persists or gets worse

Keep out of reach of children.

If swallowed, get medical help or contact a Poison Control Center right away.

Directions

- clean the affected area
- discard after a single use
- may be covered with a sterile bandage

Other information

- do not flush
- protect from freezing and avoid excessive heat
- not made with natural rubber latex

Inactive ingredient

water

Manufacturing Information

Distributed by:

Sam's West, Inc.

3500 SE Club Blvd, Bentonville, AR 72712 USA

Packaged in China with components from Taiwan

samsclub.com/membersmarkhelp

REF: SMPRT09073741

V2 RJ23SXM